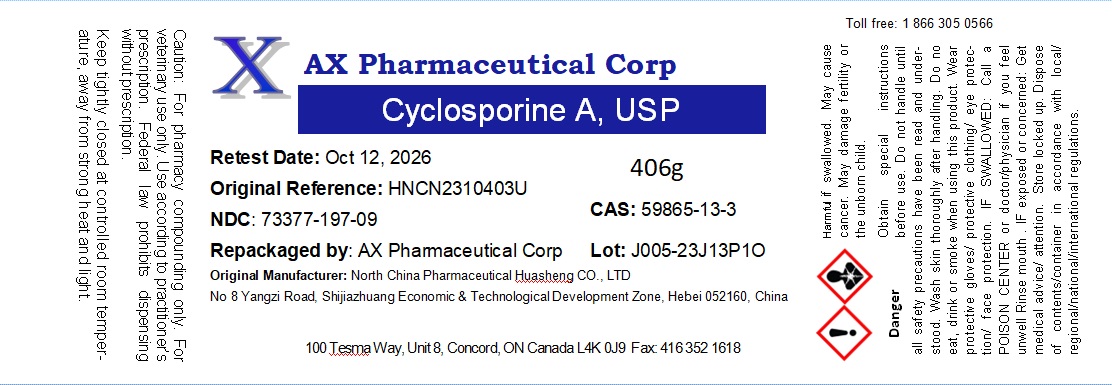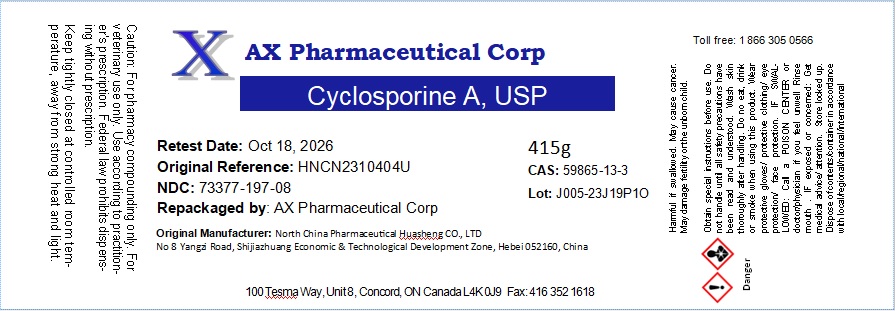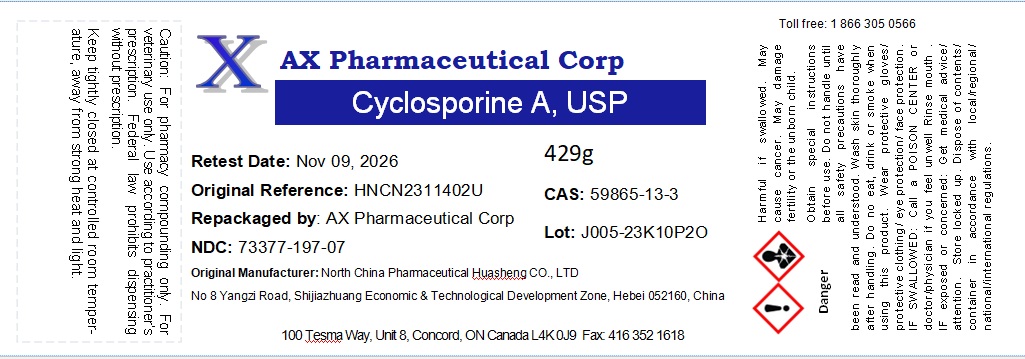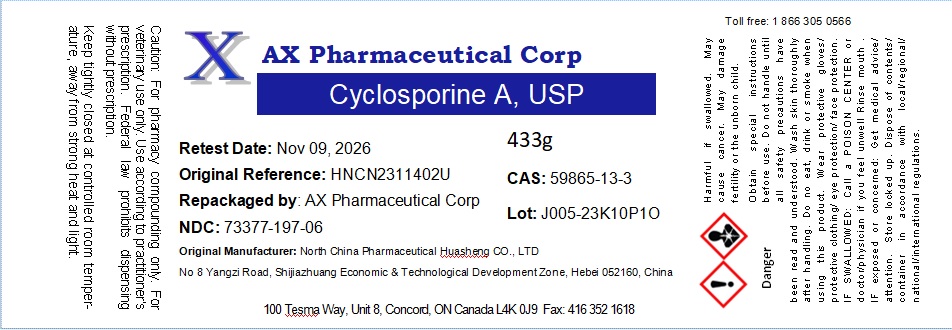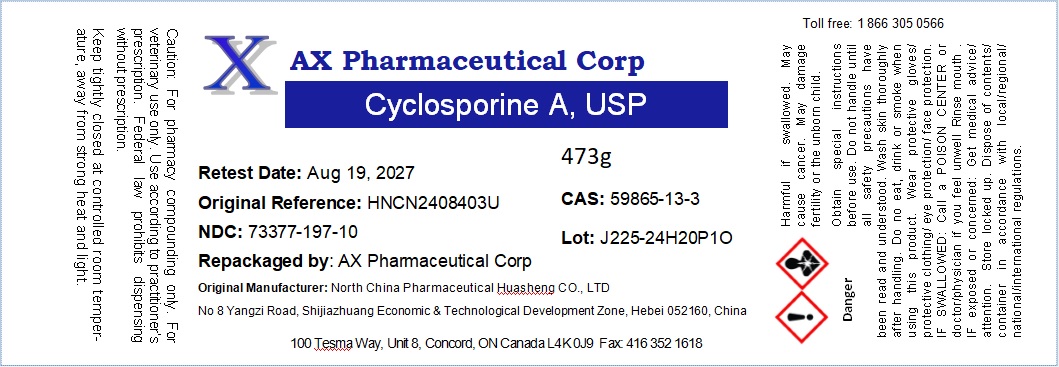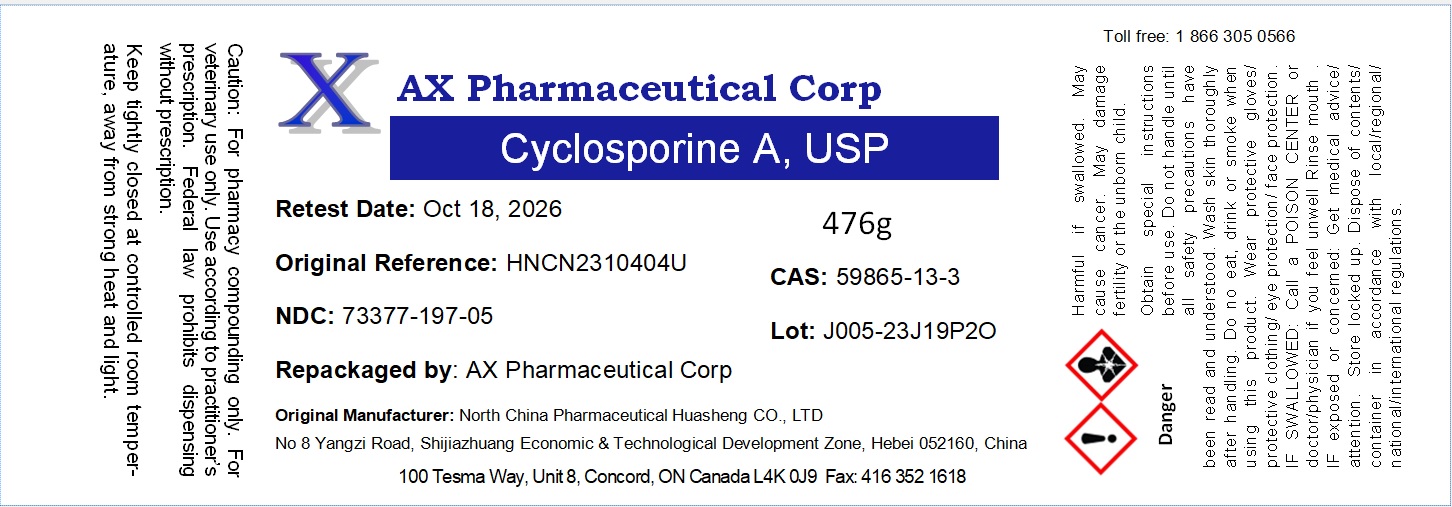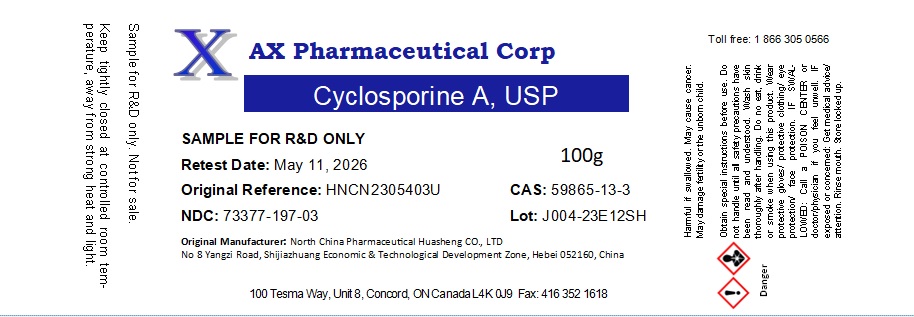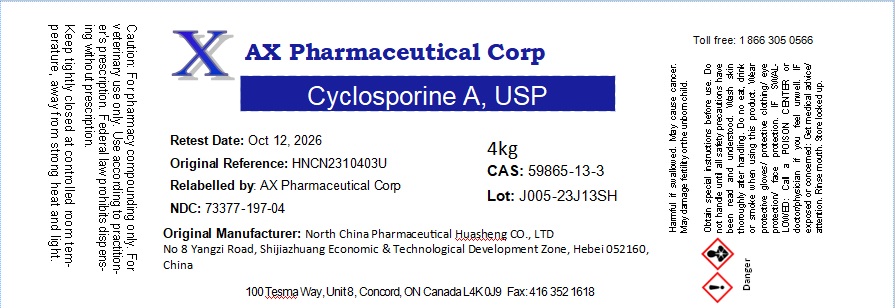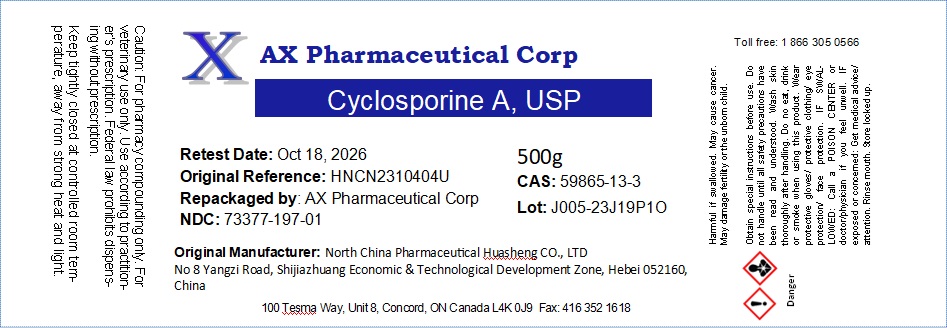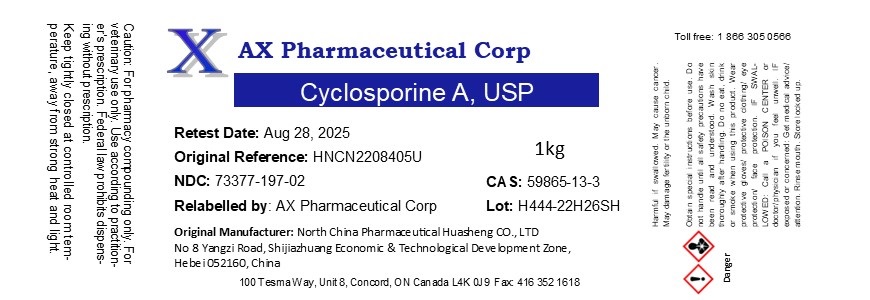 DRUG LABEL: Cyclosporine A
NDC: 73377-197 | Form: POWDER
Manufacturer: AX Pharmaceutical Corp
Category: other | Type: BULK INGREDIENT - ANIMAL DRUG
Date: 20241203

ACTIVE INGREDIENTS: CYCLOSPORINE 1 g/1 g

Cyclosporine A